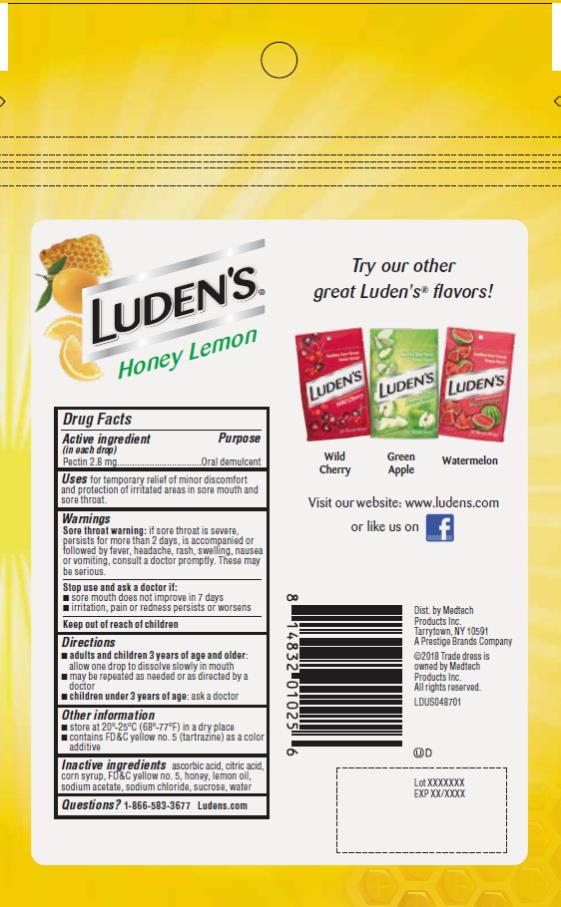 DRUG LABEL: Ludens Honey Lemon
NDC: 52183-220 | Form: LOZENGE
Manufacturer: Prestige Brands Holdings, Inc.
Category: otc | Type: HUMAN OTC DRUG LABEL
Date: 20250117

ACTIVE INGREDIENTS: PECTIN 2.8 mg/1 1
INACTIVE INGREDIENTS: ASCORBIC ACID; CITRIC ACID MONOHYDRATE; CORN SYRUP; FD&C YELLOW NO. 5; HONEY; LEMON OIL; SODIUM ACETATE; SODIUM CHLORIDE; SUCROSE; WATER

Ludens Honey Lemon

Drug Facts

Active ingredient (in each drop)

Pectin 2.8 mg

Purpose

Oral demulcent

Uses

for temporary relief of minor discomfort and protection of irritated areas in sore mouth and sore throat.

Warnings

Sore throat warning: if sore throat is severe, persists for more than 2 days, is accompanied or followed by fever, headache, rash, swelling, nausea, or vomiting, consult a doctor promptly. These may be serious.

Stop use and ask a doctor if

- sore mouth does not improve in 7 days
- irritation, pain or redness persists or worsens

Directions

- adults and children 3 years of age and older: allow one drop to dissolve slowly in mouth
  ▪ may be repeated as needed or as directed by a doctor
- children under 3 years of age: ask a doctor

Other information

- store at 20º-25ºC (68º-77ºF) in a dry place
- Contains FD&C yellow no. 5 (tartrazine) as a color additive

Inactive ingredients

ascorbic acid, citric acid, corn syrup, FD&C yellow no. 5, honey, lemon oil, sodium acetate, sodium chloride, sucrose, water

Questions?

1-866-583-3677 Ludens.com

PRINCIPAL DISPLAY PANEL

Luden’s ®

Honey Lemon

Pectin lozenge/ oral demulcent

25 Throat Drops

Luden’s ®

Honey Lemon

Pectin lozenge/ oral demulcent

90 Throat Drops